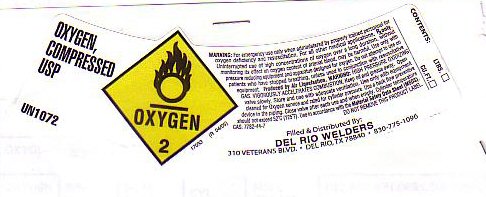 DRUG LABEL: OXYGEN
NDC: 54131-001 | Form: GAS
Manufacturer: Del Rio Welders Equipment, Inc.
Category: prescription | Type: HUMAN PRESCRIPTION DRUG LABEL
Date: 20251121

ACTIVE INGREDIENTS: OXYGEN 99 L/100 L

OXYGEN COMPRESSED LABEL

OXYGEN COMPRESSED USP UN1072

WARNING: FOR EMERGENCY USE ONLY WHEN ADMINISTERED BY PROPERLY TRAINED PERSONNEL FOR OXYGEN DEFICIENCY AND RESUSCITATION. FOR ALL OTHER MEDICAL APPLICATIONS Rx ONLY. UNINTERRUPTED USE OF HIGH CONCENTRATION OF OXYGEN OVER A LONG DURATION WITHOUT MONITORING ITS EFFECT ON OXYGEN CONTENT OF ARTERIAL BLOOD MAY BE HARMFUL. USE ONLY WITH PRESSURE REDUCING EQUIPMENT AND APPARATUS DESIGNED FOR OXYGEN. DO NOT ATTEMPT TO USE ON PATIENTS WHO HAVE STOPPED BREATHING, UNLESS USED IN CONJUNCTION WITH RESUSCITATIVE EQUIPMENT. PRODUCED BY AIR LIQUEFACTION.

WARNING: HIGH PRESSURE OXIDIZING GAS UNDER PRESSURE. VIGOROUSLY ACCELERATES COMBUSTION. KEEP OIL AND GREASE AWAY. OPEN VALVE SLOWLY. STORE AND USE WITH ADEQUATE VENTILATION. USE ONLY WITH EQUIPMENT CLEANED FOR OXYGEN SERVICE AND RATED FOR CYLINDER PRESSURE. USE A BACK FLOW PREVENTATIVE DEVICE IN THE PIPING. CLOSE VALVE AFTER EACH USE AND WHEN EMPTY. CYLINDER TEMPERATURE SHOULD NOT EXCEED 52 C (125 F) USE IN ACCORDANCE WITH THE MATERIAL SAFETY DATA SHEET (MSDS) DO NOT REMOVE THIS PRODUCT LABEL C.A.S.7782-44-7